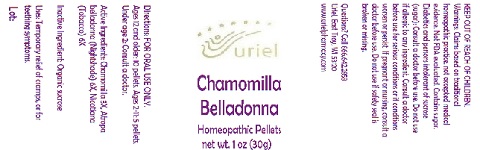 DRUG LABEL: Chamomilla Belladonna
NDC: 48951-3223 | Form: PELLET
Manufacturer: Uriel Pharmacy Inc.
Category: homeopathic | Type: HUMAN OTC DRUG LABEL
Date: 20180601

ACTIVE INGREDIENTS: TOBACCO LEAF 6 [hp_X]/1 1; MATRICARIA RECUTITA 3 [hp_X]/1 1; ATROPA BELLADONNA 6 [hp_X]/1 1
INACTIVE INGREDIENTS: SUCROSE

Chamomilla Belladonna

INDICATIONS AND USAGE

Directions: FOR ORAL USE ONLY.

DOSAGE AND ADMINISTRATION

Ages 12 and older: 10 pellets. Ages 2-11: 5 pellets. Under age 2: Consult a doctor.

ACTIVE INGREDIENT

Active Ingredients: Chamomilla 3X, Atropa belladonna (Nightshade) 6X, Nicotiana (Tobacco) 6X

Inactive Ingredient: Organic sucrose

PURPOSE

Uses: Temporary relief of cramps, or for teething symptoms.

KEEP OUT OF REACH OF CHILDREN.

WARNINGS

Warnings: Claims based on traditional homeopathic practice, not accepted medical evidence. Not FDA evaluated. Contains sugar. Diabetics and persons intolerant of sucrose (sugar): Consult a doctor before use. Do not use if allergic to any ingredient. Consult a doctor before use for serious conditions or if conditions worsen or persist. If pregnant or nursing, consult a doctor before use. Do not use if safety seal is broken or missing.

Questions? Call 866.642.2858
Uriel, East Troy, WI 53120
www.urielpharmacy.com